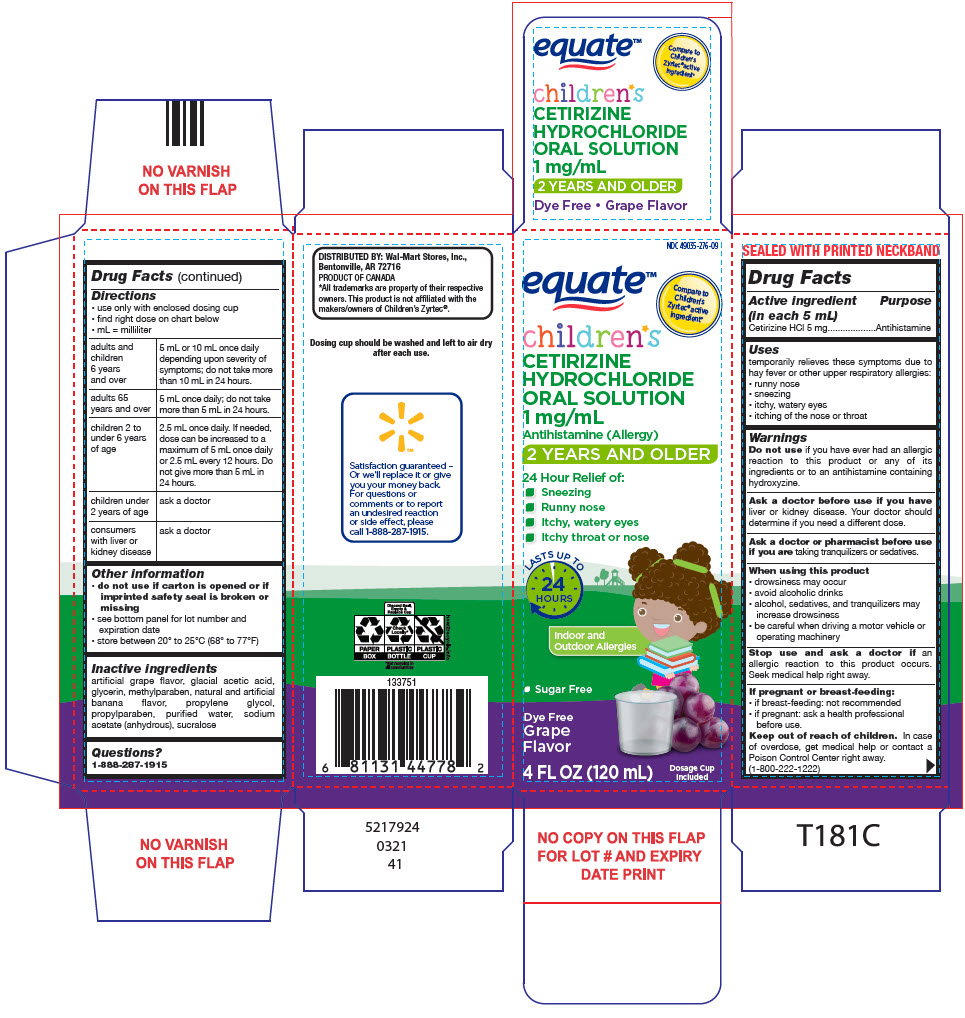 DRUG LABEL: Equate 

NDC: 49035-276 | Form: SOLUTION
Manufacturer: Wal-Mart Stores Inc
Category: otc | Type: HUMAN OTC DRUG LABEL
Date: 20250929

ACTIVE INGREDIENTS: CETIRIZINE HYDROCHLORIDE 5 mg/5 mL
INACTIVE INGREDIENTS: ACETIC ACID; GLYCERIN; METHYLPARABEN; PROPYLENE GLYCOL; PROPYLPARABEN; WATER; SODIUM ACETATE ANHYDROUS; SUCRALOSE

Equate™
Children's Allergy Relief

Drug Facts

Active ingredient (in each 5 mL)

Cetirizine HCl 5 mg

Purpose

Antihistamine

Uses

temporarily relieves these symptoms due to hay fever or other upper respiratory allergies:

- runny nose
- sneezing
- itchy, watery eyes
- itching of the nose or throat

Warnings

DO NOT USE

Do not useif you have ever had an allergic reaction to this product or any of its ingredients or to an antihistamine containing hydroxyzine.

Ask a doctor before use if you haveliver or kidney disease. Your doctor should determine if you need a different dose.

Ask a doctor or pharmacist before use if you aretaking tranquilizers or sedatives.

When using this product

- drowsiness may occur
- avoid alcoholic drinks
- alcohol, sedatives, and tranquilizers may increase drowsiness
- be careful when driving a motor vehicle or operating machinery

Stop use and ask a doctor ifan allergic reaction to this product occurs. Seek medical help right away.

If pregnant or breast-feeding

- if breast-feeding: not recommended
- if pregnant: ask a health professional before use.

Keep out of reach of children.In case of overdose, get medical help or contact a Poison Control Center right away. (1-800-222-1222)

Directions

- use only with enclosed dosing cup
- find right dose on chart below
- mL = milliliter

adults and children 6 years and over | 5 mL or 10 mL once daily depending upon severity of symptoms; do not take more than 10 mL in 24 hours.
adults 65 years and over | 5 mL once daily; do not take more than 5 mL in 24 hours.
children 2 to under 6 years of age | 2.5 mL once daily. If needed, dose can be increased to a maximum of 5 mL once daily or 2.5 mL every 12 hours. Do not give more than 5 mL in 24 hours.
children under 2 years of age | ask a doctor
consumers with liver or kidney disease | ask a doctor

Other information

- do not use if carton is opened or if imprinted safety seal is broken or missing
- see bottom panel for lot number and expiration date
- store between 20° to 25°C (68° to 77°F)

Inactive ingredients

artificial grape flavor, glacial acetic acid, glycerin, methylparaben, natural and artificial banana flavor, propylene glycol, propylparaben, purified water, sodium acetate (anhydrous), sucralose

Questions?

1-888-287-1915

DISTRIBUTED BY: Wal-Mart Stores, Inc.,
Bentonville, AR 72716

PRINCIPAL DISPLAY PANEL - 120 mL Bottle Carton

NDC 49035-276-09

equate™

Compare to
Children's
Zyrtec®active
ingredient*

children*s
CETIRIZINE
HYDROCHLORIDE
ORAL SOLUTION
1 mg/mL
Antihistamine (Allergy)

2 YEARS AND OLDER

24 Hour Relief of:

- Sneezing
- Runny nose
- Itchy, watery eyes
- Itchy throat or nose

LASTS UP TO
24
HOURS

Indoor and
Outdoor Allergies

- Sugar Free

Dye Free
Grape
Flavor

4 FL OZ (120 mL)

Dosage Cup
Included